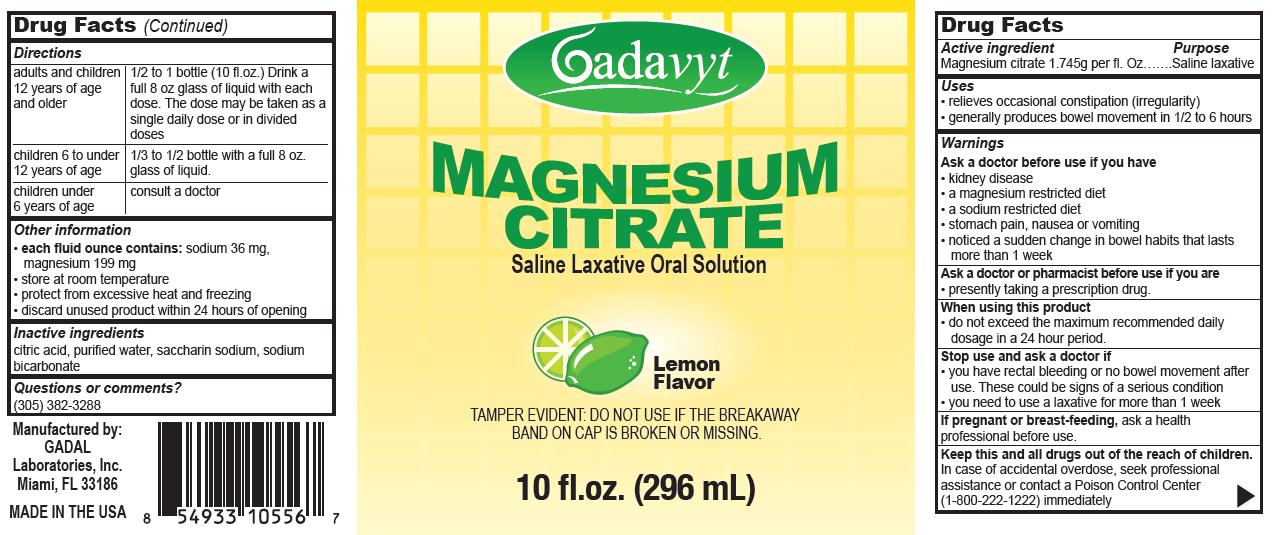 DRUG LABEL: Gadavyt
NDC: 53113-103 | Form: LIQUID
Manufacturer: Gadal Laboratories Inc
Category: otc | Type: HUMAN OTC DRUG LABEL
Date: 20121015

ACTIVE INGREDIENTS: MAGNESIUM CITRATE 1.745 g/29.6 mL
INACTIVE INGREDIENTS: CITRIC ACID MONOHYDRATE; SODIUM BICARBONATE; SACCHARIN SODIUM DIHYDRATE; WATER

Drug Facts

Active Ingredient Purpose
Magnesium citrate 1.745g per fl. Oz...... Saline Laxative

Uses

- relieves occasional constipation (irregularity)
- generally produces bowel movement in 1/2 to 6 hours

Warnings

Ask a doctor before use if you have

- kidney disease
- a magnesium restricted diet
- a sodium restricted diet
- stomach pain, nausea or vomiting
- noticed a sudden change in bowel habits that lasts more than 1 week.

Ask a doctor or pharmacist before use if you are

- presently taking a prescription drug

When using this product

- do not exceed the maximum recommended daily dosage in a 24 hour period

Stop use and ask a doctor if

- you have rectal bleeding or no bowel movement after use. These could be signs of a serious condition
- you need to use a laxative for more than 1 week

KEEP OUT OF REACH OF CHILDREN

Keep this and all drugs out of the reach of children.

In case of accidental overdose, seek professional assistance or contact a Poison Control Center (1-800-222-1222) immediately

PREGNANCY OR BREAST FEEDING

If pregnant or breast-feeding ask a health professional before use.

Directions

adults and children 12 years of age and older | 1/2 to 1 bottle (10 fl. oz.) Drink a full 8 oz glass of liquid with each dose. These dose may be taken as a single daily dose or in divided doses
children 6 to under 12 years of age | 1/3 to 1/2 bottle with a fill 8 oz glass of liquid
children under 6 years of age | consult a doctor

Other information

- each fluid once contains: sodium 36 mg, magnesium 199 mg
- store at room temperature
- protect from excessive heat and freezing
- discard unused product within 24 hours of opening

Inactive ingredients

citric acid, flavors, purified water, red 40, blue #1, saccharin sodium, sodium bicarbonate

Questions or comments?

(305) 382-3288

Gadal Laboratories Inc

Miami Fl 33186